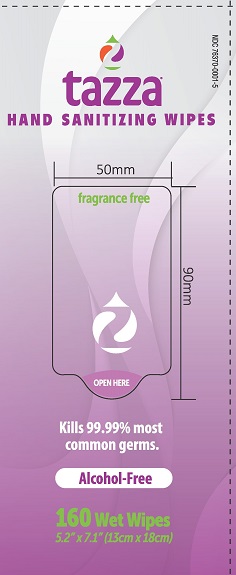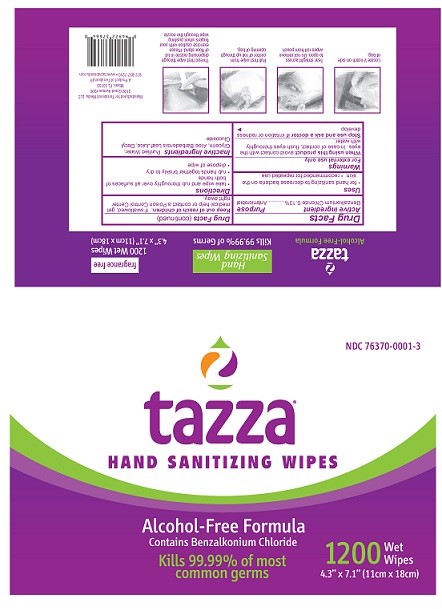 DRUG LABEL: Tazza
NDC: 76370-0001 | Form: CLOTH
Manufacturer: Tazza Brands East Inc.
Category: otc | Type: HUMAN OTC DRUG LABEL
Date: 20251217

ACTIVE INGREDIENTS: BENZALKONIUM CHLORIDE 0.13 g/100 mL
INACTIVE INGREDIENTS: WATER; GLYCERIN; ALOE VERA LEAF; DECYL GLUCOSIDE

Tazza Hand Sanitizing Wipes

Drug Facts

Active ingredient

Benzalkonium Chloride 0.13%

Purpose

Antimicrobial

Uses

- for hand sanitizing to decrease bacteria on the skin
- recommended for repeated use

Warnings

For external use only

WHEN USING

When using this productavoid contact with eyes. In case of eye contact, flush eyes with water.

Stop use and ask a doctor ifirritation or redness develop

Keep out of reach of children.If swallowed, get medical help or contact a Poison Control Center right away.

Directions

- take wipe and rub thoroughly over all surfaces of both hands
- rub hands together briskly to dry
- dispose of wipe

INACTIVE INGREDIENT

Inactive ingredientsPurified Water, Glycerin, Aloe Barbadensis Leaf Juice, Decyl Glucoside

Manufactured for Terraboost Media, LLC

3109 Grand Avenue #300

Miami, FL 33133

877-837-7210

A Product of Terraboost®

877-837-7210

www.tazzabrands.com

Cannister

NDC 76370-0001-3

tazza®

HAND SANITIZING WIPES

Alcohol-Free Formula

Contains Benzalkonium Chloride

Kills 99.99% of most common germs

1200Wet Wipes

4.3" x 7.1" ((11cm x 18cm)

Pouch

NDC 76370-0001-5

tazza®

HAND SANITIZING WIPES

fragrance free

Kills 99.99% most common germs.

Alcohol-Free

160 Wet Wipes

5.2 X 7.1" (13cm X 18cm)